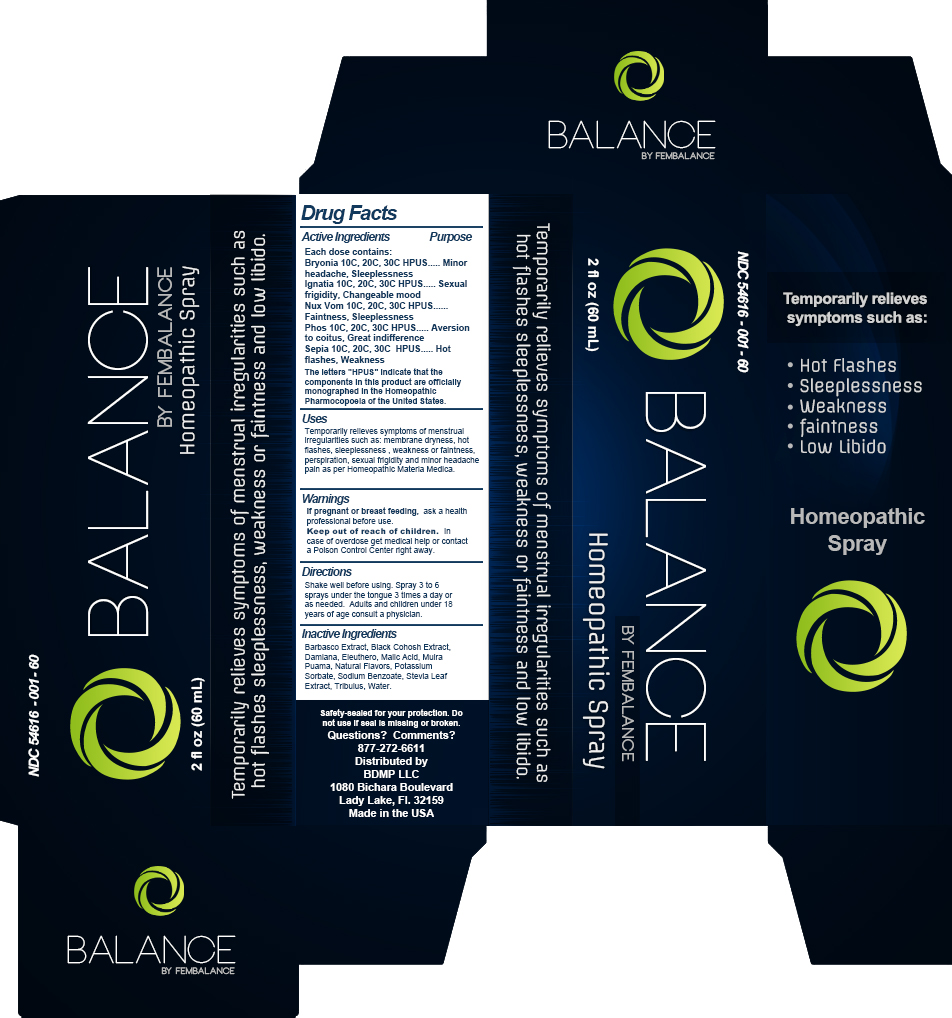 DRUG LABEL: BALANCE
                
NDC: 54616-001 | Form: SPRAY
Manufacturer: BDMP, LLC 
Category: homeopathic | Type: HUMAN OTC DRUG LABEL
Date: 20130221

ACTIVE INGREDIENTS: BRYONIA ALBA ROOT 30 [hp_C]/60 mL; STRYCHNOS IGNATII SEED 30 [hp_C]/60 mL; STRYCHNOS NUX-VOMICA SEED 30 [hp_C]/60 mL; PHOSPHORUS 30 [hp_C]/60 mL; SEPIA OFFICINALIS JUICE 30 [hp_C]/60 mL
INACTIVE INGREDIENTS: BARBASCO; BLACK COHOSH; TURNERA DIFFUSA LEAFY TWIG; ELEUTHERO; MALIC ACID; DULACIA INOPIFLORA WOOD; POTASSIUM SORBATE; SODIUM BENZOATE; STEVIA REBAUDIUNA LEAF; TRIBULUS TERRESTRIS; WATER

Active Ingredients

Each dose contains:
Bryonia 10C, 20C, 30C HPUS
Ignatia 10C, 20C, 30C HPUS
Nux Vom 10C, 20C, 30C HPUS
Phos 10C, 20C, 30C HPUS
Sepia 10C, 20C, 30C HPUS
The letters "HPUS" indicate that the components in this product are officially monographed in the Homeopathic Pharmacopoeia of the United States.

Purpose

Bryonia 10C, 20C, 30C HPUS.....................Minor headache, Sleeplessness
Ignatia 10C, 20C, 30C HPUS......................Sexual frigidity, Changeable mood
Nux Vom 10C, 20C, 30C HPUS..................Faintness, Sleeplessness
Phos 10C, 20C, 30C HPUS........................Aversion to coitus, Great indifference
Sepia 10C, 20C, 30C HPUS........................Hot flashes, Weakness

Uses

Temporarily relieves symptoms of menstrual irregularities such as: membrane dryness, hot flashes, sleeplessness, weakness or faintness, perspiration, sexual frigidity and minor headache pain as per Homeopathic Materia Medica.

Warnings

If pregnant or breast feeding, ask a health professional before use.

Keep out of reach of children.

WARNINGS

In case of overdose get medical help or contact a Poison Control Center right away.

Directions

Shake well before using. Spay 3 to 6 sprays under the tongue 3 times a day or as needed. Adults and children under 18 years of age consult a physician.

Inactive Ingredients

Barbasco Extract, Black Cohosh Extract, Damiana, Eleuthero, Malic Acid, Muira Puama,

Natural Flavors, Potassium Sorbate, Sodium Benzoate, Stevia Leaf Extract, Tribulus, Water.

STORAGE AND HANDLING

Safety-sealed for your protection. Do not use if seal is missing or broken.

Questions? Comments?

877-272-6611

Distributed by

BDMP LLC

1080 Bichara Boulevard

Lady Lake, Fl. 32159

Made in the USA

DESCRIPTION

Temporarily relieves symptoms of menstrual irregularities such as hot flashes, sleeplessness, weakness or

faintness and low libido.

Homeopathic Spray

Principal Display Panel

NDC 54616-001-00

BALANCE

BY FEMBALANCE

2 fl oz (60 mL) Homeopathic Spray

Temporarily relieves symptoms of menstrual irregularities such as

hot flashes sleeplessness, weakness or faintness and low libido.